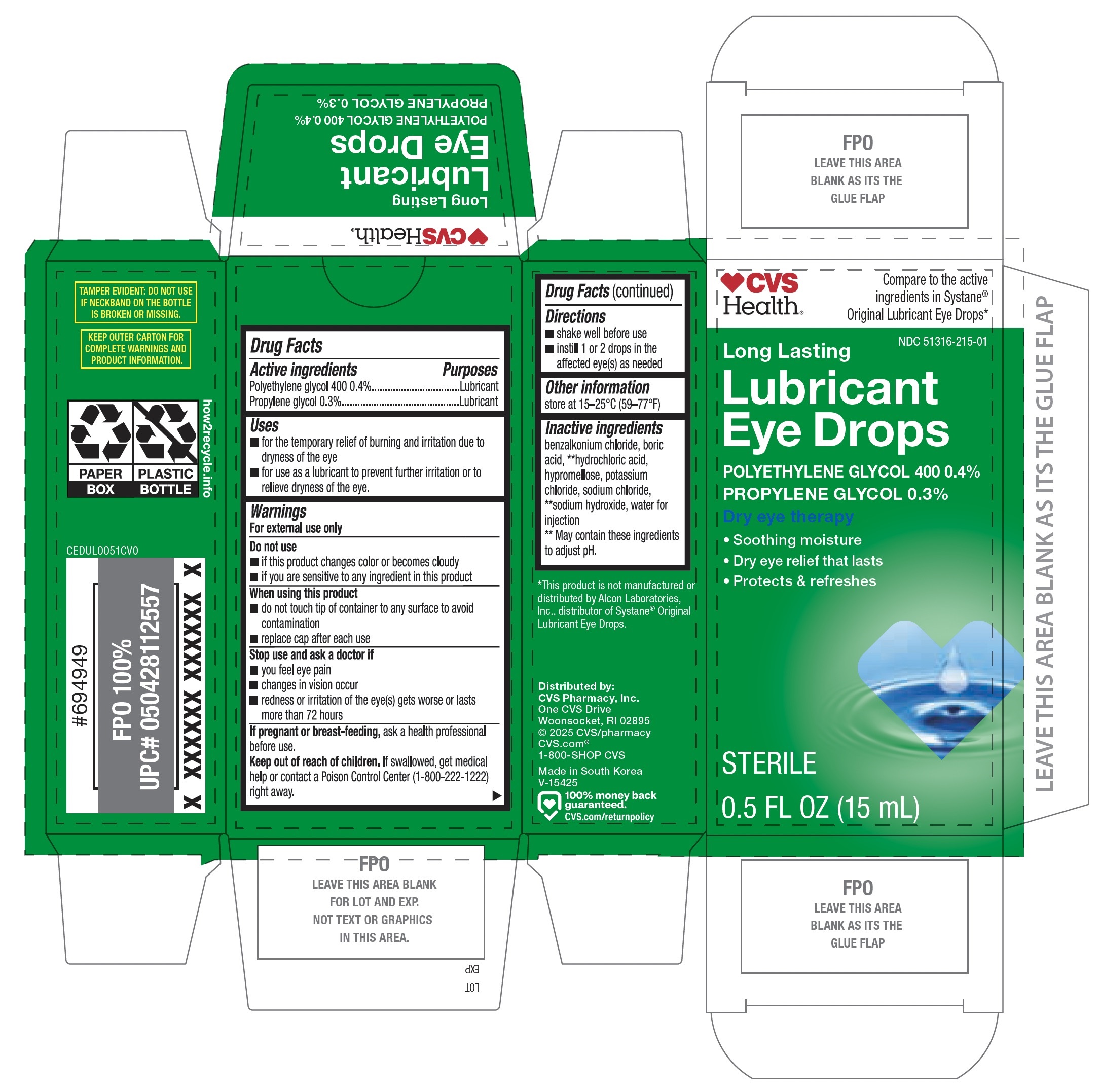 DRUG LABEL: CVS Long Lasting Lubricant Eye Drops 15mL
NDC: 51316-215 | Form: SOLUTION/ DROPS
Manufacturer: CVS Pharmacy, Inc.
Category: otc | Type: HUMAN OTC DRUG LABEL
Date: 20251230

ACTIVE INGREDIENTS: POLYETHYLENE GLYCOL 400 0.4 g/100 mL; PROPYLENE GLYCOL 0.3 g/100 mL
INACTIVE INGREDIENTS: HYDROCHLORIC ACID; BENZALKONIUM CHLORIDE; HYPROMELLOSE, UNSPECIFIED; BORIC ACID; SODIUM CHLORIDE; POTASSIUM CHLORIDE; SODIUM HYDROXIDE; WATER

CVS Long Lasting Lubricant Eye Drops 15mL (PLD)

Active ingredients

Polyethylene glycol 400 0.4%

Propylene glycol 0.3%

Purposes

Lubricant

Lubricant

Uses

- for the temporary relief of burning and irritation due to dryness of the eye
- for the use as a lubricant to prevent further irritation or to relieve dryness of the eye

Warnings

For external use only

Do not use

- if this product changes color or becomes cloudy
- if you are sensitive to any ingredient in this product

When using this product

- do not touch tip of container to any surface to avoid contamination
- replace cap after each use

Stop use and ask a doctor if

- you feel eye pain
- changes in vision occur
- redness or irritation of the eye(s) gets worse or lasts more than 72 hours

If pregnant or breast-feeding,

ask a health professional before use.

Keep out of reach of children.

If swallowed, get medical help or contact a Poison Control Center (1-800-222-1222) right away.

Directions

- shake well before use
- instill 1 or 2 drops in the affected eye(s) as needed

Other information

store at 15-25°C (59-77°F)

Inactive ingredients

benzalkonium chloride, boric acid, **hydrochloric acid, hypromellose, potassium chloride, sodium chloride, **sodium hydroxide, water for injection

**May contain these ingredients to adjust pH.